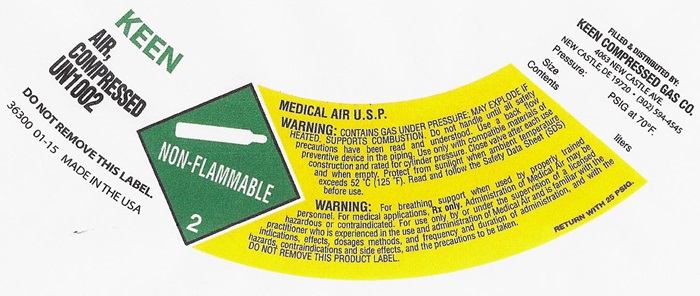 DRUG LABEL: MEDICAL AIR
NDC: 48273-007 | Form: GAS
Manufacturer: Keen Compressed Gas Co. Inc.
Category: prescription | Type: HUMAN PRESCRIPTION DRUG LABEL
Date: 20181025

ACTIVE INGREDIENTS: OXYGEN 21 L/100 L
INACTIVE INGREDIENTS: NITROGEN

AIR COMPRESSED USP LABEL

KEEN

AIR, COMPRESSED USP UN1002

DO NOT REMOVE THIS LABEL

36300-01-15 MADE IN THE USA

NON-FLAMMABLE GAS

MEDICAL AIR, U.S.P.

WARNING: CONTAINS GAS UNDER PRESSURE; MAY EXPLODE IF HEATED, SUPPORTS COMBUSTION. Do not handle until all safety precautions have been read and understood. Use a backflow preventive device I the piping. Use only with equipment of compatible materials of construction and rated for cylinder pressure. Close valve after each use and when empty. Protect from sunlight when ambient temperature exceeds 52°C (125°F). Read and follow the Safety Data Sheet (SDS) before use.

WARNING: For breathing support when used by properly trained personnel. For medical applications. Rx only. Administration of Medical Air may be hazardous or contraindicated. For use only by or under the supervision of a licensed practitioner who is experienced in the use and administration of Medical Air and is familiar with the indications, effects, dosages, methods, and frequency and duration of administration, and with the hazards, contraindications and side effects and the precautions to be taken.

DO NOT REMOVE THIS PRODUCT LABEL

RETURN WITH 25 PSIG

FILLED & DISTRIBUTED BY:

KEEN COMPRESSED GAS CO.

4063 NEW CASTLE AVE.

NEW CASTELE, de 19720 • (302) 594-4545

Pressure: PSIG at 70OF

Size

Contents liters